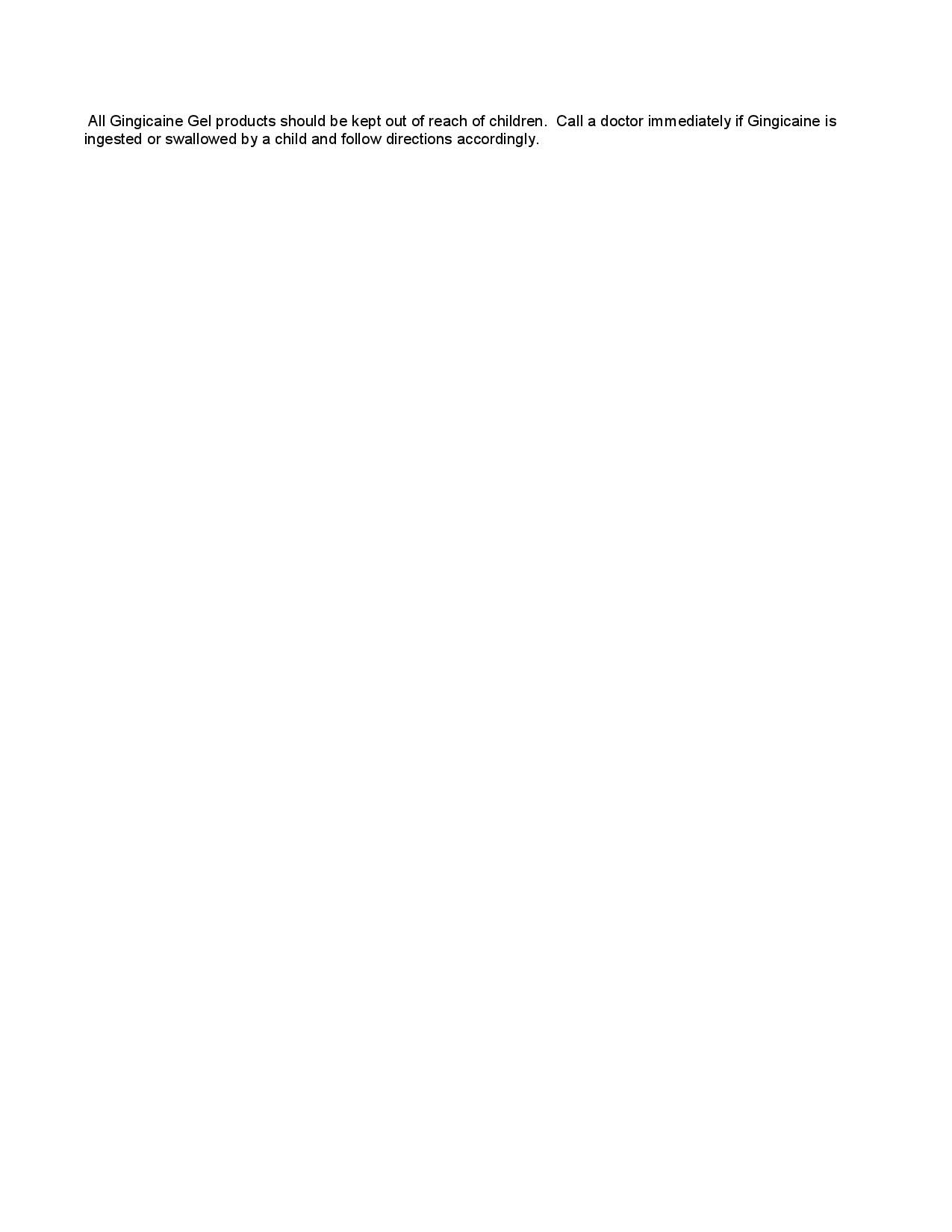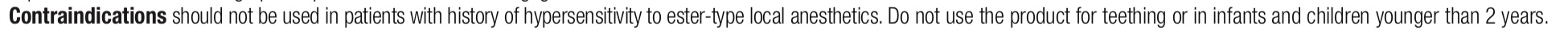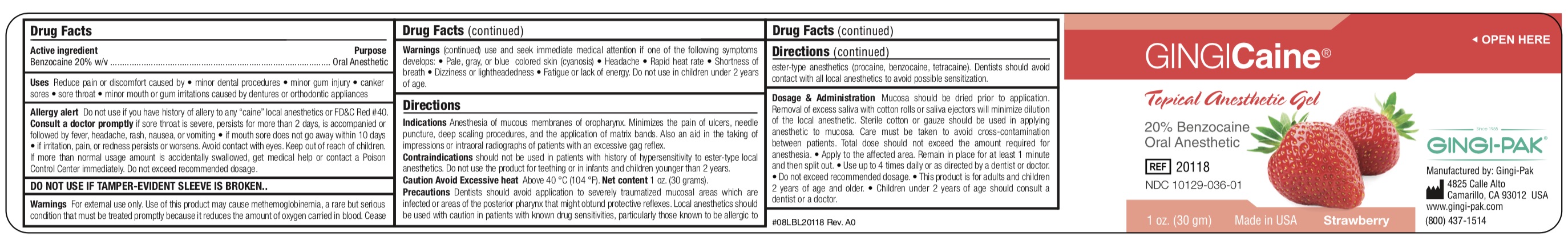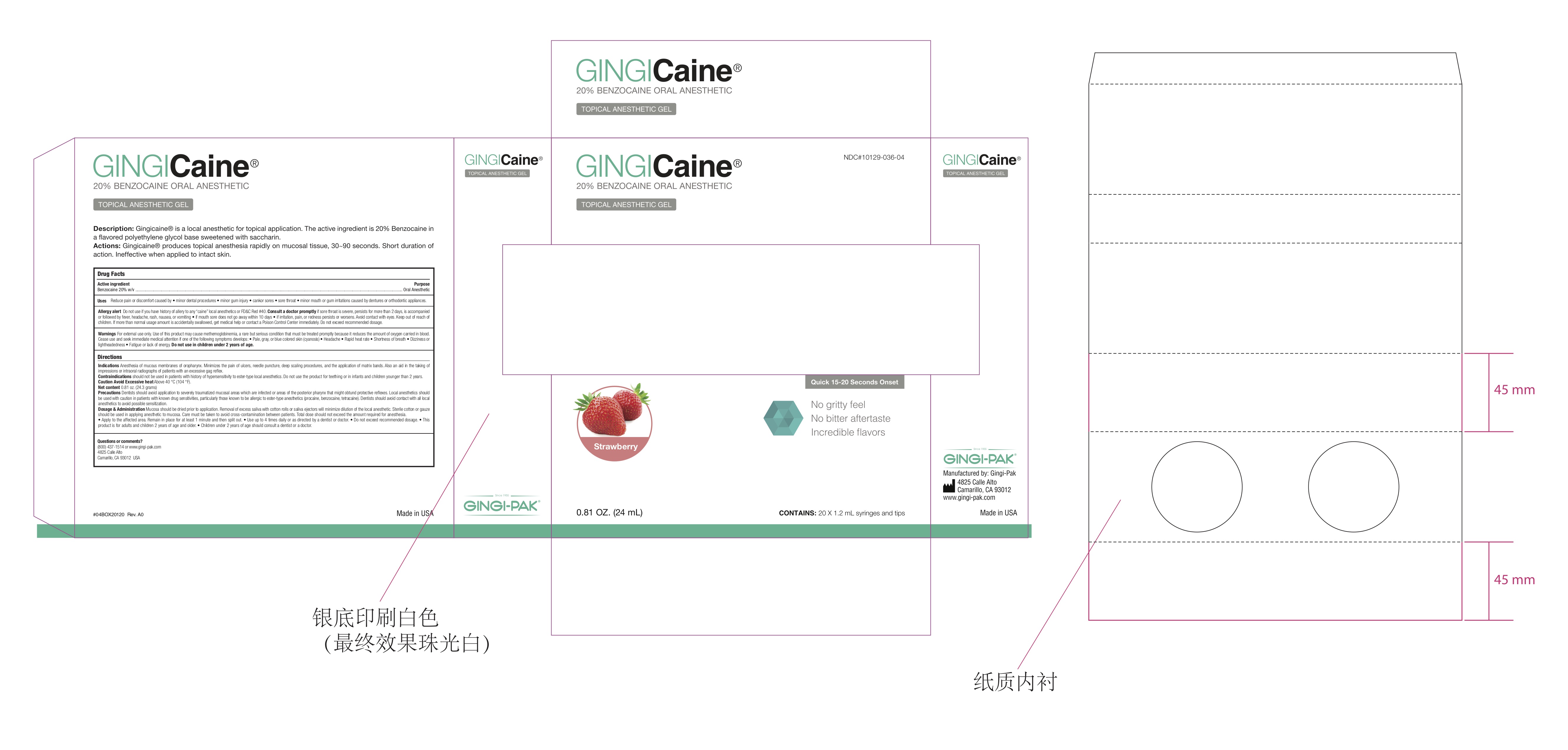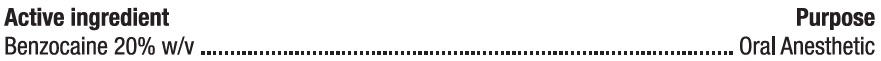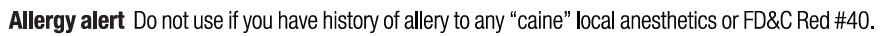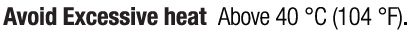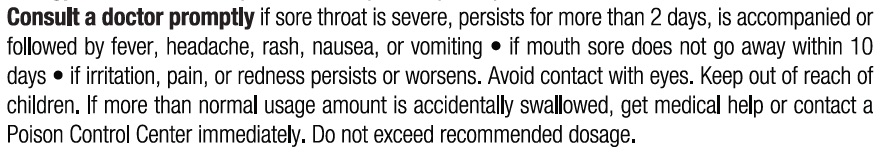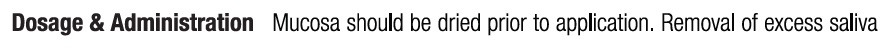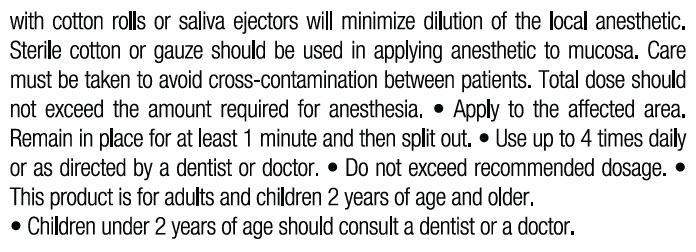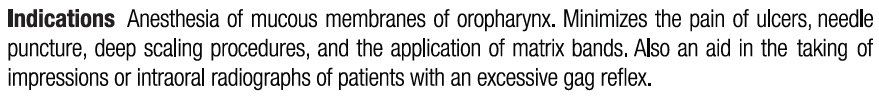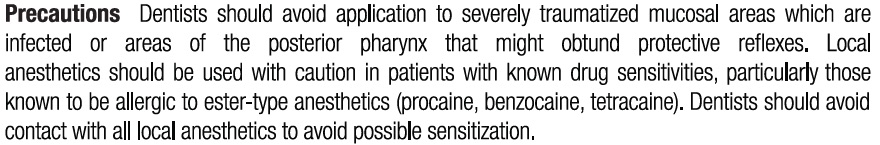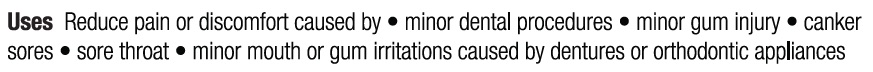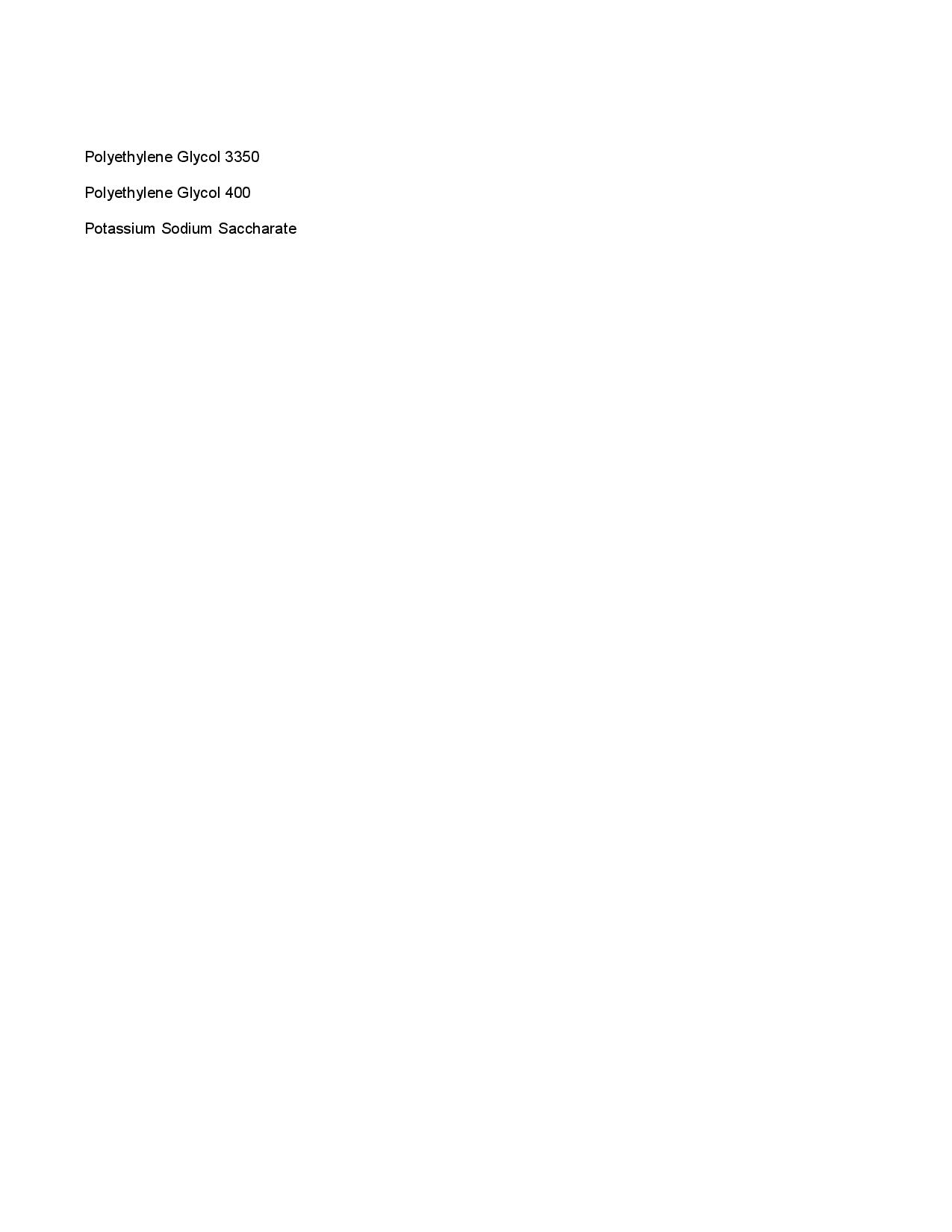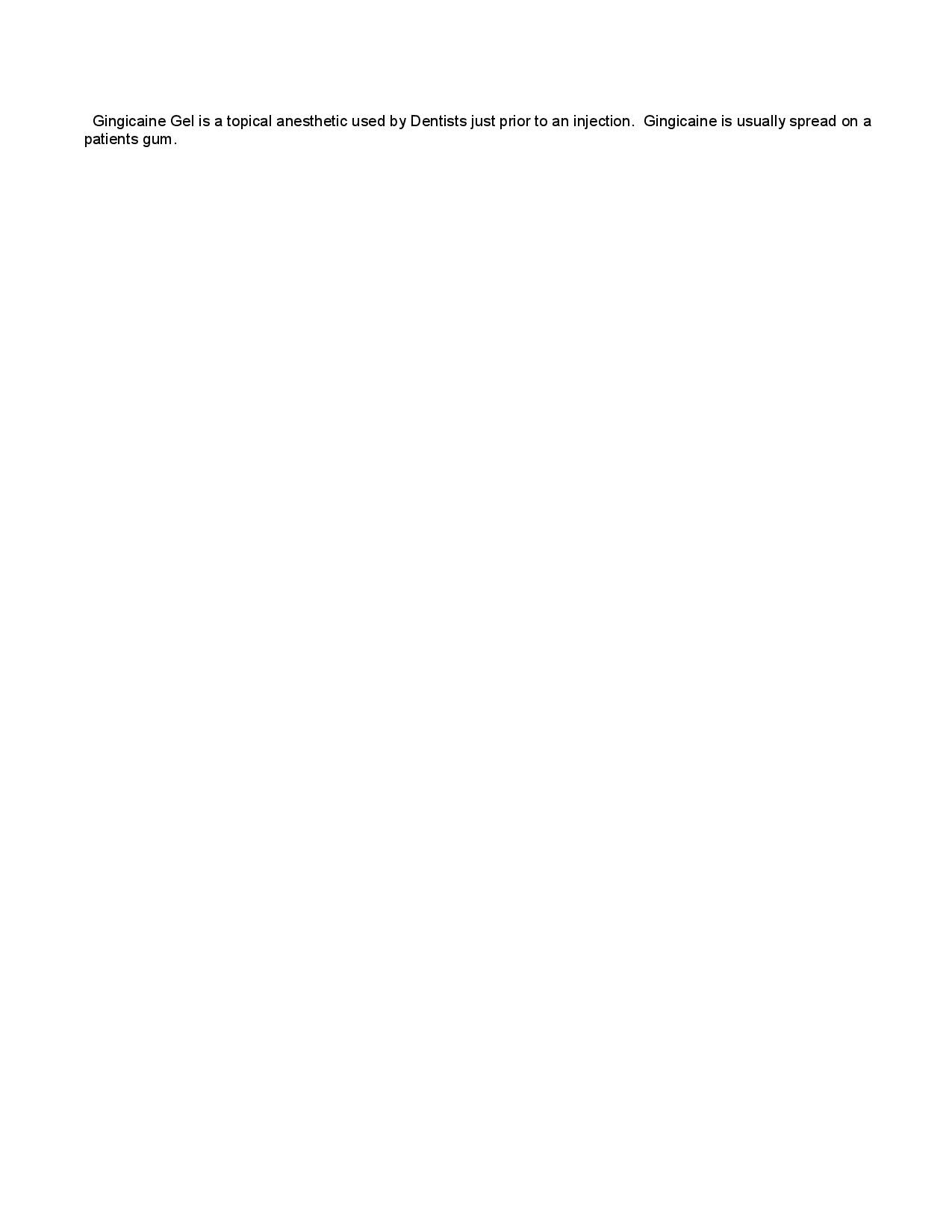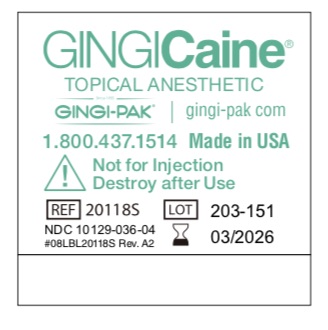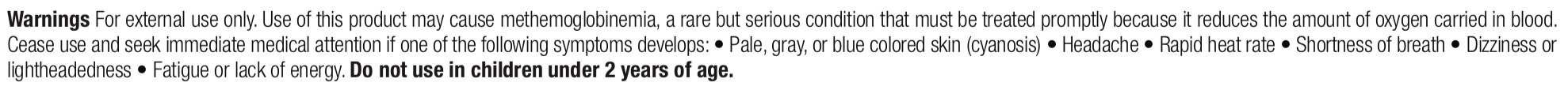 DRUG LABEL: Gingicaine Gel Strawberry
NDC: 10129-036 | Form: GEL
Manufacturer: Gingi-Pak a Division of the Belport
Category: otc | Type: HUMAN OTC DRUG LABEL
Date: 20231227

ACTIVE INGREDIENTS: BENZOCAINE 200 mg/1 1
INACTIVE INGREDIENTS: POTASSIUM SODIUM SACCHARATE 20 mg/1 1; POLYETHYLENE GLYCOL 400 520 mg/1 1; POLYETHYLENE GLYCOL 3350 260 mg/1 1

Gingicaine Gel, Strawberry